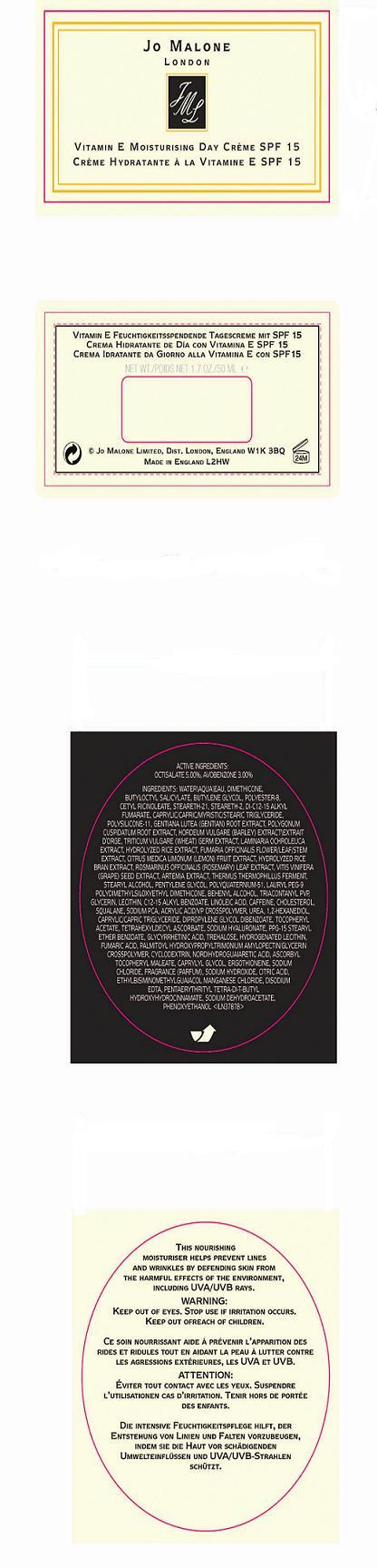 DRUG LABEL: VITAMIN E DAY
NDC: 62874-005 | Form: CREAM
Manufacturer: JO MALONE LTD
Category: otc | Type: HUMAN OTC DRUG LABEL
Date: 20110701

ACTIVE INGREDIENTS: OCTISALATE 5.0 mL/100 mL; AVOBENZONE 3.0 mL/100 mL
INACTIVE INGREDIENTS: WATER; DIMETHICONE; BUTYLOCTYL SALICYLATE; POLYESTER-10; MEDIUM-CHAIN TRIGLYCERIDES; GENTIANA LUTEA ROOT; BARLEY; WHEAT GERM; LAMINARIA OCHROLEUCA; FUMARIA OFFICINALIS FLOWERING TOP; LEMON; RICE BRAN; ROSEMARY; VITIS VINIFERA SEED; STEARYL ALCOHOL; PENTYLENE GLYCOL; DOCOSANOL; GLYCERIN; LECITHIN, SOYBEAN; ALKYL (C12-15) BENZOATE; LINOLEIC ACID; CAFFEINE; CHOLESTEROL; SQUALANE; SODIUM PYRROLIDONE CARBOXYLATE; 1,2-HEXANEDIOL; .ALPHA.-TOCOPHEROL ACETATE, D-; TETRAHEXYLDECYL ASCORBATE; HYALURONATE SODIUM; ENOXOLONE; TREHALOSE; HYDROGENATED SOYBEAN LECITHIN; MASOPROCOL; CAPRYLYL GLYCOL; ERGOTHIONEINE; SODIUM CHLORIDE; SODIUM HYDROXIDE; CITRIC ACID MONOHYDRATE; EDETATE DISODIUM; PENTAERYTHRITOL TETRAKIS(3-(3,5-DI-TERT-BUTYL-4-HYDROXYPHENYL)PROPIONATE); SODIUM DEHYDROACETATE; PHENOXYETHANOL

ACTIVE INGREDIENTS: OCTISALATE 5.00% [] AVOBENZONE 3.00%

INACTIVE INGREDIENT

INGREDIENTS: WATER [] DIMETHICONE [] BUTYLOCTYL SALICYLATE [] BUTYLENE GLYCOL [] POLYESTER-8 [] CETYL RICINOLEATE [] STEARETH-21 [] STEARETH-2 [] DI-C12-15 ALKYL FUMARATE [] CAPRYLIC/CAPRIC/MYRISTIC/STEARIC TRIGLYCERIDE [] POLYSILICONE-11 [] GENTIANA LUTEA (GENTIAN) ROOT EXTRACT [] POLYGONUM CUSPIDATUM ROOT EXTRACT [] HORDEUM VULGARE (BARLEY) EXTRACT\EXTRAIT D'ORGE [] TRITICUM VULGARE (WHEAT) GERM EXTRACT [] LAMINARIA OCHROLEUCA EXTRACT [] HYDROLYZED RICE EXTRACT [] FUMARIA OFFICINALIS FLOWER/LEAF/STEM EXTRACT [] CITRUS MEDICA LIMONUM (LEMON) FRUIT EXTRACT [] HYDROLYZED RICE BRAN EXTRACT [] ROSMARINUS OFFICINALIS (ROSEMARY) LEAF EXTRACT [] VITIS VINIFERA (GRAPE) SEED EXTRACT [] ARTEMIA EXTRACT [] THERMUS THERMOPHILLUS FERMENT [] STEARYL ALCOHOL [] PENTYLENE GLYCOL [] POLYQUATERNIUM-51 [] LAURYL PEG-9 POLYDIMETHYLSILOXYETHYL DIMETHICONE [] BEHENYL ALCOHOL [] TRIACONTANYL PVP [] GLYCERIN [] LECITHIN [] C12-15 ALKYL BENZOATE [] LINOLEIC ACID [] CAFFEINE [] CHOLESTEROL [] SQUALANE [] SODIUM PCA [] ACRYLIC ACID/VP CROSSPOLYMER [] UREA [] 1,2-HEXANEDIOL [] CAPRYLIC/CAPRIC TRIGLYCERIDE [] DIPROPYLENE GLYCOL DIBENZOATE [] TOCOPHERYL ACETATE [] TETRAHEXYLDECYL ASCORBATE [] SODIUM HYALURONATE [] PPG-15 STEARYL ETHER BENZOATE [] GLYCYRRHETINIC ACID [] TREHALOSE [] HYDROGENATED LECITHIN [] FUMARIC ACID [] PALMITOYL HYDROXYPROPYLTRIMONIUM AMYLOPECTIN/GLYCERIN CROSSPOLYMER [] CYCLODEXTRIN [] NORDIHYDROGUAIARETIC ACID [] ASCORBYL TOCOPHERYL MALEATE [] CAPRYLYL GLYCOL [] ERGOTHIONEINE [] SODIUM CHLORIDE [] FRAGRANCE (PARFUM) [] SODIUM HYDROXIDE [] CITRIC ACID [] ETHYLBISIMINOMETHYLGUAIACOL MANGANESE CHLORIDE [] DISODIUM EDTA [] PENTAERYTHRITYL TETRA-DI-T-BUTYL HYDROXYHYDROCINNAMATE [] SODIUM DEHYDROACETATE [] PHENOXYETHANOL

WARNINGS

WARNING: KEEP OUT OF EYES. STOP USE IF IRRITATION OCCURS. KEEP OUT OF REACH OF CHILDREN.

PACKAGE LABEL

PRINCIPAL DISPLAY PANEL:

JO MALONE

VITAMIN E DAY CREAM

NET WT. 1.7 OZ/50ML

DISTR JO MALONE LTD

LONDON, ENGLAND W1K 3BQ